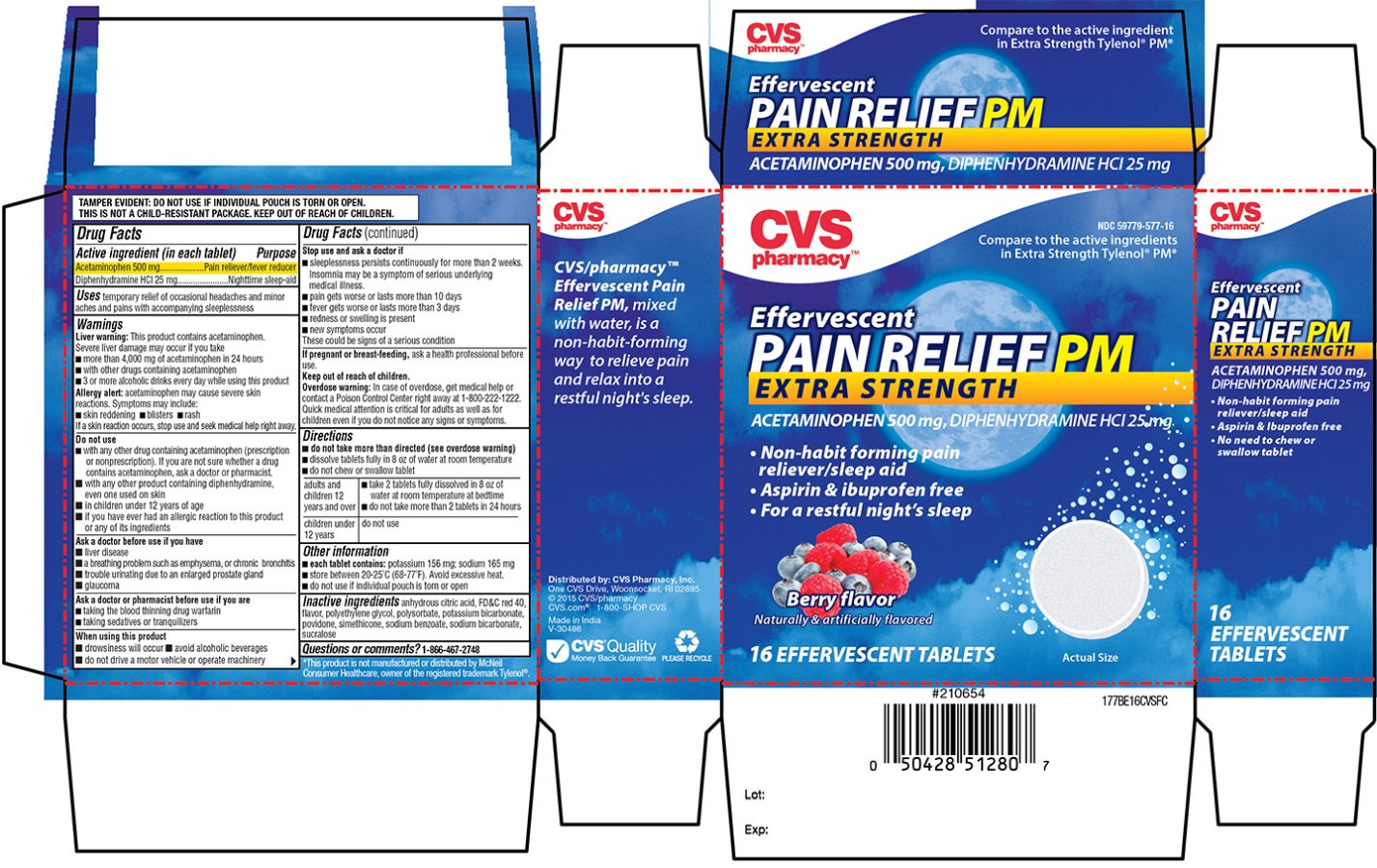 DRUG LABEL: CVS
NDC: 59779-577 | Form: TABLET
Manufacturer: CVS Pharmacy
Category: otc | Type: HUMAN OTC DRUG LABEL
Date: 20150202

ACTIVE INGREDIENTS: ACETAMINOPHEN 500 mg/1 1; DIPHENHYDRAMINE HYDROCHLORIDE 25 mg/1 1
INACTIVE INGREDIENTS: ANHYDROUS CITRIC ACID; FD&C RED NO. 40; POLYETHYLENE GLYCOLS; POLYSORBATE 80; POTASSIUM BICARBONATE; POVIDONES; DIMETHICONE; SODIUM BENZOATE; SODIUM BICARBONATE; SUCRALOSE

CVS Effervescent Pain Relief PM

Drug Facts

Active ingredient (in each tablet)

Acetaminophen 500 mg

Diphenhydramine 25 mg

Purpose

Pain Reliever/fever reducer

Nighttime sleep-aid

Uses

temporary relief of occasional headaches and minor aches and pain with accompanying sleeplessness

Warnings

Liver warning

This product contains acetaminophen. Severe liver damage can occur if you take

- more than 4,000 mg of acetaminophen in 24 hours
- with other drugs containing acetaminophen
- 3 or more alcoholic drinks every day while using this product

Do not use

- with any other drug containing acetaminophen (prescription or nonprescription). If you are not sure whether a drug contains acetaminophen, ask a doctor or pharmacist.
- with any other product containing diphenhydramine, even one used on skin
- in children under 12 years of age
- if you ever had an allergic reaction to this product or any of its ingredients

Ask a doctor before use if you have

- liver disease
- a breathing problem such as emphysema, or chronic bronchitis
- trouble urinating due to enlarged prostate gland
- glaucoma

Ask a doctor or pharmacist before use if you are

- taking the blood thinning drug warfarin
- taking sedatives or tranquilizers

When Using this product

- drowsiness will occur
- avoid alcoholic beverages
- do not drive or operate machinery

Stop use and ask a doctor if

- sleeplessness persists continuously for more than 2 weeks. Insomnia may be a symptom of serious underlying medical illness.
- pain gets worse or lasts more than 10 days
- fever gets worse or lasts more than 3 days
- new symptoms occur
- redness or swelling is present
- new symptoms occur

These could be signs of a serious condition.

If pregnant or breast-feeding,

ask a health professional before use.

Keep out of reach of children.

Overdose warning

In case of overdose, get medical help or contact a Poison Control Center right away at 1-800-222-1222. Quick medical attention is critical for adults as well as for children even if you do not notice any signs or symptoms.

Directions

- do not take more than directed (see Overdose warning)
- dissolve tablets fully in 8 oz of water at room temperature
- do not chew or swallow tablet

Adults and children 12 years and over | - take 2 tablets fully dissolved in 8 oz of water at room temperature at bedtime - do not take more than 2 tablets in 24 hours
children under 12 years | do not use

Other information

- each tablet contains: potassium 156 mg; sodium 165 mg
- store between 20-25°C (68-77°F). Avoid excessive heat.
- do not use if individual pouch is torn or open

Inactive ingredients

anhydrous citric acid, FD&C red 40, flavor, polyethylene glycol, polysorbate, potassium bicarbonate, povidone, simethicone, sodium benzoate, sodium bicarbonate, sucralose

Questions or comments

1-866-467-2748

Distributed By: CVS Pharmacy, Inc.

One CVS Drive, Woonsocket RI 02895

CVS.com

1-800-SHOP CVS

*This product is not manufactured or distributed by McNeil Consumer Healthcare, owner of the registered trademark Tylenol®.

Tamper Evident: Do not use if individual pouch is torn or open. This is not a child resistant package. Keep out of reach of children.

PRINCIPAL DISPLAY PANEL

Effervescent Pain Relief PM

Extra Strength

Acetaminophen 500mg, Diphenhydramine HCl 25mg

Compare to the active ingredient in Extra Strength Tylenol® PM**

Non-habit forming pain reliever/sleep aid

Aspirin & Ibuprofen free

For a restful night's sleep

No need to chew or swallow tablet

Berry flavor
16 Effervescent Tablets